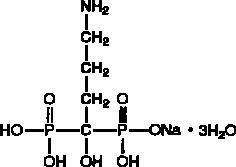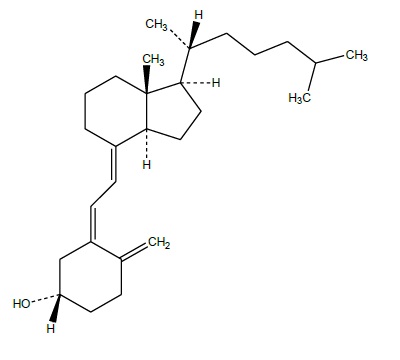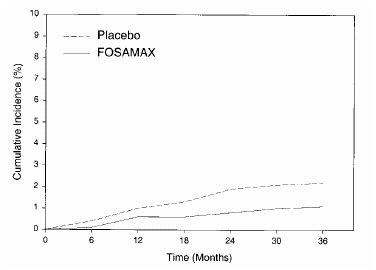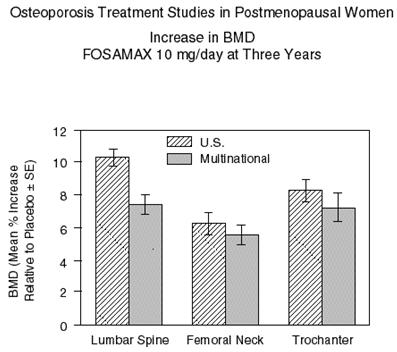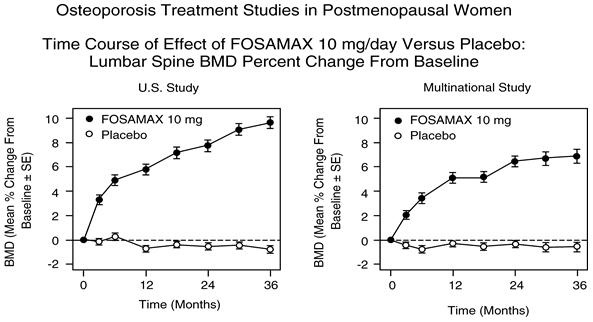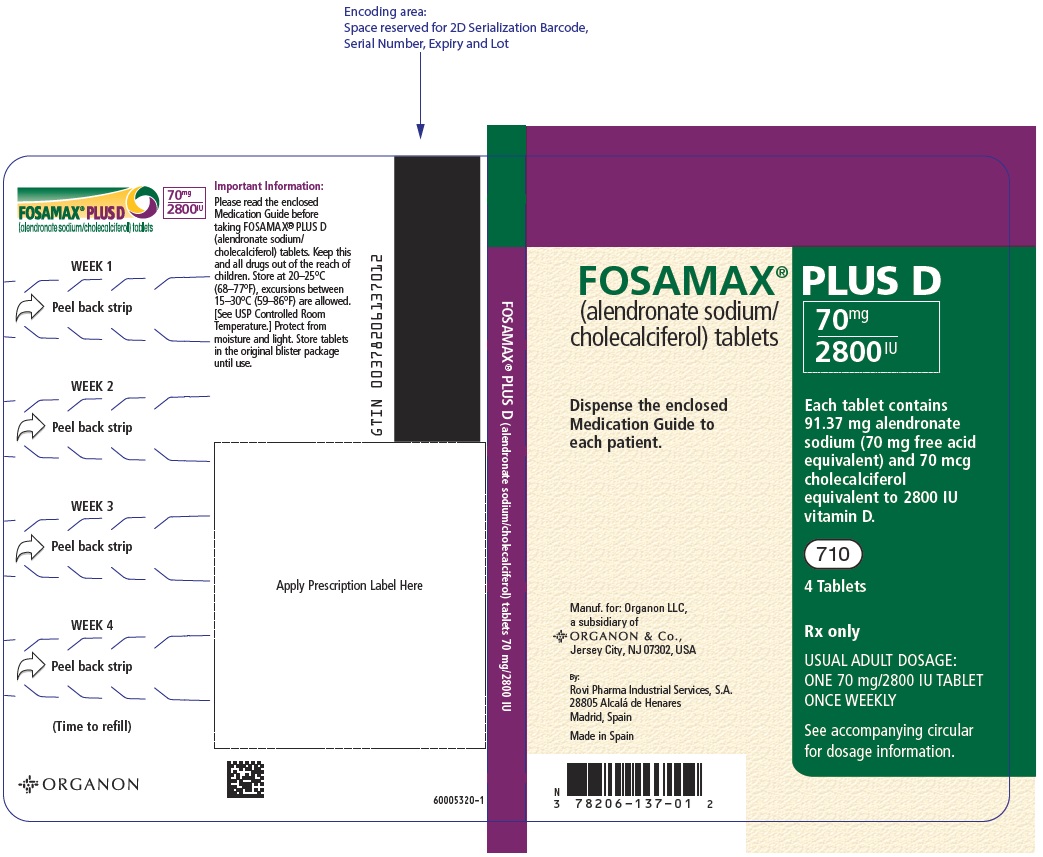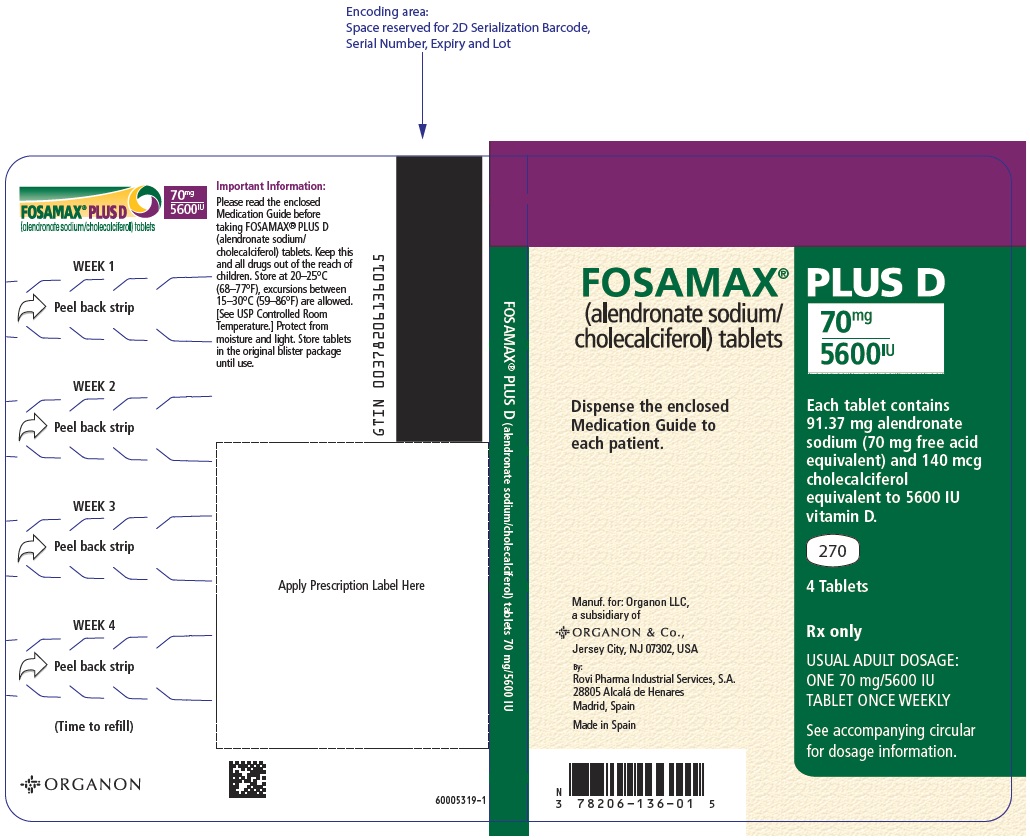 DRUG LABEL: FOSAMAX PLUS D
NDC: 78206-137 | Form: TABLET
Manufacturer: Organon LLC
Category: prescription | Type: HUMAN PRESCRIPTION DRUG LABEL
Date: 20260203

ACTIVE INGREDIENTS: ALENDRONATE SODIUM 70 mg/1 1; CHOLECALCIFEROL 2800 [iU]/1 1
INACTIVE INGREDIENTS: BUTYLATED HYDROXYTOLUENE; SILICON DIOXIDE; CROSCARMELLOSE SODIUM; GELATIN, UNSPECIFIED; ANHYDROUS LACTOSE; MAGNESIUM STEARATE; MICROCRYSTALLINE CELLULOSE; SUCROSE; STARCH, CORN; MEDIUM-CHAIN TRIGLYCERIDES; SODIUM ALUMINOSILICATE

HIGHLIGHTS OF PRESCRIBING INFORMATION

These highlights do not include all the information needed to use FOSAMAX PLUS D safely and effectively. See full prescribing information for FOSAMAX PLUS D.
FOSAMAX® PLUS D
(alendronate sodium/cholecalciferol) tablets
Initial U.S. Approval: 2005

RECENT MAJOR CHANGES

Warnings and Precautions, Atypical Fractures Including Femoral Fractures (5.5) | 2/2026

1 INDICATIONS AND USAGE

FOSAMAX PLUS D is a combination of a bisphosphonate and vitamin D indicated for:

- Treatment of osteoporosis in postmenopausal women (1.1)
- Treatment to increase bone mass in men with osteoporosis (1.2)

Limitations of use:

- FOSAMAX PLUS D alone should not be used to treat vitamin D deficiency. (1.3)
- Optimal duration of use has not been determined. For patients at low-risk for fracture, consider drug discontinuation after 3 to 5 years of use. (1.3)

2 DOSAGE AND ADMINISTRATION

- 70 mg alendronate/2800 international units vitamin D3 or 70 mg alendronate/5600 international units vitamin D3 tablet once weekly. (2.1, 2.2)
- Instruct patients to: (2.3)
  - Swallow tablets whole with 6-8 ounces plain water at least 30 minutes before the first food, drink, or medication of the day.
  - Not lie down for at least 30 minutes after taking FOSAMAX PLUS D and until after food.

3 DOSAGE FORMS AND STRENGTHS

Tablets: 70 mg/2800 international units and 70 mg/5600 international units (3)

4 CONTRAINDICATIONS

- Abnormalities of the esophagus which delay emptying such as stricture or achalasia (4, 5.1)
- Inability to stand/sit upright for at least 30 minutes (2.3, 4, 5.1)
- Hypocalcemia (4, 5.2)
- Hypersensitivity to any component of this product (4, 6.2)

5 WARNINGS AND PRECAUTIONS

- Upper Gastrointestinal Adverse Reactions can occur. Instruct patients to follow dosing instructions. Discontinue if new or worsening symptoms occur. (5.1)
- Hypocalcemia can worsen and must be corrected prior to use. (5.2)
- Severe Bone, Joint, Muscle Pain may occur. Discontinue use if severe symptoms develop. (5.3)
- Osteonecrosis of the Jaw has been reported. (5.4)
- Atypical Fractures Including Femoral Fractures have been reported. Patients with new thigh or groin pain should be evaluated to rule out a femoral fracture. Risk/benefit of continuing bisphosphonate therapy should be re-evaluated in these patients and interruption of bisphosphonate therapy should be considered. (5.5)

6 ADVERSE REACTIONS

Most common adverse reactions (greater than or equal to 3%) for alendronate are: abdominal pain, acid regurgitation, constipation, diarrhea, dyspepsia, musculoskeletal pain, nausea. (6.1)

To report SUSPECTED ADVERSE REACTIONS, contact Organon LLC, a subsidiary of Organon & Co., at 1-844-674-3200 or FDA at 1-800-FDA-1088 or www.fda.gov/medwatch.

7 DRUG INTERACTIONS

- Calcium supplements/antacids or oral medications containing multivalent cations interfere with absorption of alendronate. (2.3, 7.1)
- Use caution when co-prescribing aspirin/nonsteroidal anti-inflammatory drugs that may worsen gastrointestinal irritation. (7.2, 7.3)
- Some drugs may impair the absorption or increase the catabolism of cholecalciferol (vitamin D3). Additional vitamin D supplementation should be considered. (7.4, 7.5, 12.3)

8 USE IN SPECIFIC POPULATIONS

- Pregnancy: Discontinue when pregnancy is recognized. (8.1)
- FOSAMAX PLUS D is not indicated for use in pediatric patients. (8.4)
- FOSAMAX PLUS D is not recommended in patients with severe renal impairment (creatinine clearance less than 35 mL/min). (5.6, 8.6)

FULL PRESCRIBING INFORMATION

1 INDICATIONS AND USAGE

1.1 Treatment of Osteoporosis in Postmenopausal Women

FOSAMAX® PLUS D is indicated for the treatment of osteoporosis in postmenopausal women. In postmenopausal women, FOSAMAX PLUS D increases bone mass and reduces the incidence of fractures, including those of the hip and spine (vertebral compression fractures). [See Clinical Studies (14.1).]

1.2 Treatment to Increase Bone Mass in Men with Osteoporosis

FOSAMAX PLUS D is indicated for treatment to increase bone mass in men with osteoporosis [see Clinical Studies (14.2)].

1.3 Important Limitations of Use

FOSAMAX PLUS D alone should not be used to treat vitamin D deficiency.

The optimal duration of use has not been determined. The safety and effectiveness of FOSAMAX PLUS D for the treatment of osteoporosis are based on clinical data of four years duration. All patients on bisphosphonate therapy should have the need for continued therapy re-evaluated on a periodic basis. Patients at low-risk for fracture should be considered for drug discontinuation after 3 to 5 years of use. Patients who discontinue therapy should have their risk for fracture re-evaluated periodically.

2 DOSAGE AND ADMINISTRATION

2.1 Treatment of Osteoporosis in Postmenopausal Women

The recommended dosage is one 70 mg alendronate/2800 international units vitamin D3 or one 70 mg alendronate/5600 international units vitamin D3 tablet once weekly. For most osteoporotic women, the appropriate dose is FOSAMAX PLUS D (70 mg alendronate/5600 international units vitamin D3) once weekly.

2.2 Treatment to Increase Bone Mass in Men with Osteoporosis

The recommended dosage is one 70 mg alendronate/2800 international units vitamin D3 or one 70 mg alendronate/5600 international units vitamin D3 tablet once weekly. For most osteoporotic men, the appropriate dose is FOSAMAX PLUS D (70 mg alendronate/5600 international units vitamin D3) once weekly.

2.3 Important Administration Instructions

Instruct patients to do the following:

- Take FOSAMAX PLUS D at least one-half hour before the first food, beverage, or medication of the day with plain water only [see Patient Counseling Information (17)]. Other beverages (including mineral water), food, and some medications are likely to reduce the absorption of alendronate [see Drug Interactions (7.1)]. Waiting less than 30 minutes, or taking FOSAMAX PLUS D with food, beverages (other than plain water) or other medications will lessen the effect of alendronate by decreasing its absorption into the body.
- Take FOSAMAX PLUS D upon arising for the day. To facilitate delivery to the stomach and thus reduce the potential for esophageal irritation, a FOSAMAX PLUS D tablet should be swallowed with a full glass of water (6-8 ounces). Patients should not lie down for at least 30 minutes and until after their first food of the day. FOSAMAX PLUS D should not be taken at bedtime or before arising for the day. Failure to follow these instructions may increase the risk of esophageal adverse experiences [see Warnings and Precautions (5.1) and Patient Counseling Information (17)].

2.4 Recommendations for Calcium and Vitamin D Supplementation

Instruct patients to take supplemental calcium if dietary intake is inadequate [see Warnings and Precautions (5.2)]. Patients at increased risk for vitamin D insufficiency (e.g., over the age of 70 years, nursing home bound, or chronically ill) may need additional vitamin D supplementation. Patients with gastrointestinal malabsorption syndromes may require higher doses of vitamin D supplementation and measurement of 25-hydroxyvitamin D should be considered.

The recommended intake of vitamin D is 400-800 international units daily. FOSAMAX PLUS D 70 mg/2800 international units and 70 mg/5600 international units are intended to provide seven days' worth of 400 and 800 international units daily vitamin D in a single, once-weekly dose, respectively.

2.5 Administration Instructions for Missed Doses

If a once-weekly dose of FOSAMAX PLUS D is missed, instruct patients to take one tablet on the morning after they remember. They should not take two tablets on the same day but should return to taking one tablet once a week, as originally scheduled on their chosen day.

3 DOSAGE FORMS AND STRENGTHS

- 70 mg/2800 international units tablets are white to off-white, modified capsule-shaped tablets with code 710 on one side and an outline of a bone image on the other.
- 70 mg/5600 international units tablets are white to off-white, modified rectangle-shaped tablets with code 270 on one side and an outline of a bone image on the other.

4 CONTRAINDICATIONS

FOSAMAX PLUS D is contraindicated in patients with the following conditions:

- Abnormalities of the esophagus which delay esophageal emptying such as stricture or achalasia [see Warnings and Precautions (5.1)]
- Inability to stand or sit upright for at least 30 minutes [see Dosage and Administration (2.3), Warnings and Precautions (5.1)]
- Hypocalcemia [see Warnings and Precautions (5.2)]
- Hypersensitivity to any component of this product. Hypersensitivity reactions including urticaria and angioedema have been reported [see Adverse Reactions (6.2)].

5 WARNINGS AND PRECAUTIONS

5.1 Upper Gastrointestinal Adverse Reactions

FOSAMAX PLUS D, like other bisphosphonates administered orally, may cause local irritation of the upper gastrointestinal mucosa. Because of these possible irritant effects and a potential for worsening of the underlying disease, caution should be used when FOSAMAX PLUS D is given to patients with active upper gastrointestinal problems (such as known Barrett's esophagus, dysphagia, other esophageal diseases, gastritis, duodenitis, or ulcers).

Esophageal adverse experiences, such as esophagitis, esophageal ulcers and esophageal erosions, occasionally with bleeding and rarely followed by esophageal stricture or perforation, have been reported in patients receiving treatment with oral bisphosphonates including FOSAMAX PLUS D. In some cases these have been severe and required hospitalization. Physicians should therefore be alert to any signs or symptoms signaling a possible esophageal reaction and patients should be instructed to discontinue FOSAMAX PLUS D and seek medical attention if they develop dysphagia, odynophagia, retrosternal pain or new or worsening heartburn.

The risk of severe esophageal adverse experiences appears to be greater in patients who lie down after taking oral bisphosphonates including FOSAMAX PLUS D and/or who fail to swallow oral bisphosphonates including FOSAMAX PLUS D with the recommended full glass (6-8 ounces) of water, and/or who continue to take oral bisphosphonates including FOSAMAX PLUS D after developing symptoms suggestive of esophageal irritation. Therefore, it is very important that the full dosing instructions are provided to, and understood by, the patient [see Dosage and Administration (2.3)]. In patients who cannot comply with dosing instructions due to mental disability, therapy with FOSAMAX PLUS D should be used under appropriate supervision.

There have been post-marketing reports of gastric and duodenal ulcers with oral bisphosphonate use, some severe and with complications, although no increased risk was observed in controlled clinical trials [see Adverse Reactions (6.2)].

5.2 Mineral Metabolism

Alendronate Sodium

Hypocalcemia must be corrected before initiating therapy with FOSAMAX PLUS D [see Contraindications (4)]. Other disorders affecting mineral metabolism (such as vitamin D deficiency) should also be effectively treated. In patients with these conditions, serum calcium and symptoms of hypocalcemia should be monitored during therapy with FOSAMAX PLUS D.

Presumably due to the effects of alendronate on increasing bone mineral, small, asymptomatic decreases in serum calcium and phosphate may occur.

Cholecalciferol

FOSAMAX PLUS D alone should not be used to treat vitamin D deficiency (commonly defined as 25-hydroxyvitamin D level below 9 ng/mL). Patients at increased risk for vitamin D insufficiency may require higher doses of vitamin D supplementation [see Dosage and Administration (2.4)]. Patients with gastrointestinal malabsorption syndromes may require higher doses of vitamin D supplementation and measurement of 25-hydroxyvitamin D should be considered.

Vitamin D3 supplementation may worsen hypercalcemia and/or hypercalciuria when administered to patients with diseases associated with unregulated overproduction of 1,25 dihydroxyvitamin D (e.g., leukemia, lymphoma, sarcoidosis). Urine and serum calcium should be monitored in these patients.

5.3 Musculoskeletal Pain

In post-marketing experience, severe and occasionally incapacitating bone, joint, and/or muscle pain has been reported in patients taking bisphosphonates that are approved for the prevention and treatment of osteoporosis [see Adverse Reactions (6.2)]. This category of drugs includes alendronate. Most of the patients were postmenopausal women. The time to onset of symptoms varied from one day to several months after starting the drug. Discontinue use if severe symptoms develop. Most patients had relief of symptoms after stopping. A subset had recurrence of symptoms when rechallenged with the same drug or another bisphosphonate.

In placebo-controlled clinical studies of FOSAMAX, the percentages of patients with these symptoms were similar in the FOSAMAX and placebo groups.

5.4 Osteonecrosis of the Jaw

Osteonecrosis of the jaw (ONJ), which can occur spontaneously, is generally associated with tooth extraction and/or local infection with delayed healing, and has been reported in patients taking bisphosphonates, including FOSAMAX PLUS D. Known risk factors for osteonecrosis of the jaw include invasive dental procedures (e.g., tooth extraction, dental implants, boney surgery), diagnosis of cancer, concomitant therapies (e.g., chemotherapy, corticosteroids, angiogenesis inhibitors), poor oral hygiene, and co-morbid disorders (e.g., periodontal and/or other pre-existing dental disease, anemia, coagulopathy, infection, ill-fitting dentures). The risk of ONJ may increase with duration of exposure to bisphosphonates.

For patients requiring invasive dental procedures, discontinuation of bisphosphonate treatment may reduce the risk for ONJ. Clinical judgment of the treating physician and/or oral surgeon should guide the management plan of each patient based on individual benefit/risk assessment.

Patients who develop osteonecrosis of the jaw while on bisphosphonate therapy should receive care by an oral surgeon. In these patients, extensive dental surgery to treat ONJ may exacerbate the condition. Discontinuation of bisphosphonate therapy should be considered based on individual benefit/risk assessment.

5.5 Atypical Fractures Including Femoral Fractures

Atypical, low-energy, or low trauma fractures of the femoral shaft have been reported during treatment with bisphosphonates, including alendronate, in patients with osteoporosis. Atypical femur and other fractures most commonly occur with minimal or no trauma to the affected area. These fractures occurred anywhere in the femoral shaft from just below the lesser trochanter to above the supracondylar flare and are transverse or short oblique in orientation without evidence of comminution. Atypical fractures of other bones have also been reported. They may be bilateral. These fractures can also occur in osteoporotic patients who have not been treated with bisphosphonates. Concomitant treatment with glucocorticoid may also induce these fractures.

Prodromal pain in the affected area, usually presenting as dull, aching thigh pain, weeks to months before a complete fracture occurs was reported by patients.

Any patient with a history of bisphosphonate exposure who presents with thigh or groin pain should be suspected of having an atypical fracture and should be evaluated to rule out an incomplete femur fracture. Bony pain in other locations should also be considered for evaluation of atypical fracture. Patients presenting with an atypical fracture should also be assessed for symptoms and signs of fracture in the contralateral limb. Risk/benefit of continuing bisphosphonate therapy should be re-evaluated in these patients and interruption of bisphosphonate therapy should be considered.

5.6 Renal Impairment

FOSAMAX PLUS D is not recommended for patients with creatinine clearance less than 35 mL/min.

6 ADVERSE REACTIONS

The following clinically significant adverse drug reactions are described elsewhere in the labeling:

- Upper Gastrointestinal Adverse Reactions [see Warnings and Precautions (5.1)]
- Mineral Metabolism [see Warnings and Precautions (5.2)]
- Musculoskeletal Pain [see Warnings and Precautions (5.3)]
- Osteonecrosis of the Jaw [see Warnings and Precautions (5.4)]
- Atypical Fractures Including Femoral Fractures [see Warnings and Precautions (5.5)]
- Renal Impairment [see Warnings and Precautions (5.6)]

6.1 Clinical Trials Experience

Because clinical trials are conducted under widely varying conditions, adverse reaction rates observed in the clinical trials of a drug cannot be directly compared to rates in the clinical trials of another drug and may not reflect the rates observed in clinical practice.

FOSAMAX

Treatment of Osteoporosis in Postmenopausal Women

FOSAMAX Daily

The safety of FOSAMAX in the treatment of postmenopausal osteoporosis was assessed in four clinical trials that enrolled 7453 women aged 44-84 years. Study 1 and Study 2 were identically designed, three-year, placebo-controlled, double-blind, multicenter studies (United States and Multinational; n=994); Study 3 was the three-year vertebral fracture cohort of the Fracture Intervention Trial [FIT] (n=2027); and Study 4 was the four-year clinical fracture cohort of FIT (n=4432). Overall, 3620 patients were exposed to placebo and 3432 patients exposed to FOSAMAX. Patients with pre-existing gastrointestinal disease and concomitant use of non-steroidal anti-inflammatory drugs were included in these clinical trials. In Study 1 and Study 2 all women received 500 mg elemental calcium as carbonate. In Study 3 and Study 4 all women with dietary calcium intake less than 1000 mg per day received 500 mg calcium and 250 international units Vitamin D per day.

Among patients treated with alendronate 10 mg or placebo in Study 1 and Study 2, and all patients in Study 3 and Study 4, the incidence of all-cause mortality was 1.8% in the placebo group and 1.8% in the FOSAMAX group. The incidence of serious adverse event was 30.7% in the placebo group and 30.9% in the FOSAMAX group. The percentage of patients who discontinued the study due to any clinical adverse event was 9.5% in the placebo group and 8.9% in the FOSAMAX group. Adverse reactions from these studies considered by the investigators as possibly, probably, or definitely drug related in greater than or equal to 1% of patients treated with either FOSAMAX or placebo are presented in Table 1.

Table 1: Osteoporosis Treatment Studies in Postmenopausal Women Adverse Reactions Considered Possibly, Probably, or Definitely Drug Related by the Investigators and Reported in Greater Than or Equal to 1% of Patients
 | United States/Multinational Studies |  | Fracture Intervention Trial
 | FOSAMAX [10 mg/day for three years] % (n=196) | Placebo % (n=397) | FOSAMAX [5 mg/day for 2 years and 10 mg/day for either 1 or 2 additional years] % (n=3236) | Placebo % (n=3223)
Gastrointestinal abdominal pain nausea dyspepsia constipation diarrhea flatulence acid regurgitation esophageal ulcer vomiting dysphagia abdominal distention gastritis | 6.6 3.6 3.6 3.1 3.1 2.6 2.0 1.5 1.0 1.0 1.0 0.5 | 4.8 4.0 3.5 1.8 1.8 0.5 4.3 0.0 1.5 0.0 0.8 1.3 | 1.5 1.1 1.1 0.0 0.6 0.2 1.1 0.1 0.2 0.1 0.0 0.6 | 1.5 1.5 1.2 0.2 0.3 0.3 0.9 0.1 0.3 0.1 0.0 0.7
Musculoskeletal musculoskeletal (bone, muscle or joint) pain muscle cramp | 4.1 0.0 | 2.5 1.0 | 0.4 0.2 | 0.3 0.1
Nervous System/Psychiatric headache dizziness | 2.6 0.0 | 1.5 1.0 | 0.2 0.0 | 0.2 0.1
Special Senses taste perversion | 0.5 | 1.0 | 0.1 | 0.0

Rash and erythema have occurred.

Gastrointestinal Adverse Reactions: One patient treated with FOSAMAX (10 mg/day), who had a history of peptic ulcer disease and gastrectomy and who was taking concomitant aspirin, developed an anastomotic ulcer with mild hemorrhage, which was considered drug related. Aspirin and FOSAMAX were discontinued and the patient recovered. In the Study 1 and Study 2 populations, 49-54% had a history of gastrointestinal disorders at baseline, and 54-89% used nonsteroidal anti-inflammatory drugs or aspirin at some time during the studies. [See Warnings and Precautions (5.1).]

Laboratory Test Findings: In double-blind, multicenter, controlled studies, asymptomatic, mild, and transient decreases in serum calcium and phosphate were observed in approximately 18% and 10%, respectively, of patients taking FOSAMAX versus approximately 12% and 3% of those taking placebo. However, the incidences of decreases in serum calcium to less than 8.0 mg/dL (2.0 mM) and serum phosphate to less than or equal to 2.0 mg/dL (0.65 mM) were similar in both treatment groups.

FOSAMAX Once-Weekly

The safety of FOSAMAX 70 mg once weekly for the treatment of postmenopausal osteoporosis was assessed in a one-year, double-blind, multicenter study comparing FOSAMAX 70 mg once weekly and FOSAMAX 10 mg daily. The overall safety and tolerability profiles of once weekly FOSAMAX 70 mg and FOSAMAX 10 mg daily were similar. The adverse reactions considered by the investigators as possibly, probably, or definitely drug related in greater than or equal to 1% of patients in either treatment group are presented in Table 2.

Table 2: Osteoporosis Treatment Studies in Postmenopausal Women Adverse Reactions Considered Possibly, Probably, or Definitely Drug Related by the Investigators and Reported in Greater Than or Equal to 1% of Patients
 | Once Weekly FOSAMAX 70 mg % (n=519) | FOSAMAX 10 mg/day % (n=370)
Gastrointestinal abdominal pain dyspepsia acid regurgitation nausea abdominal distention constipation flatulence gastritis gastric ulcer | 3.7 2.7 1.9 1.9 1.0 0.8 0.4 0.2 0.0 | 3.0 2.2 2.4 2.4 1.4 1.6 1.6 1.1 1.1
Musculoskeletal musculoskeletal (bone, muscle, joint) pain muscle cramp | 2.9 0.2 | 3.2 1.1

Concomitant Use With Estrogen/Hormone Replacement Therapy

In two studies (of one and two years' duration) of postmenopausal osteoporotic women (total: n=853), the safety and tolerability profile of combined treatment with FOSAMAX 10 mg once daily and estrogen ± progestin (n=354) was consistent with those of the individual treatments.

Osteoporosis in Men

In two placebo-controlled, double-blind, multicenter studies in men (a two-year study of FOSAMAX 10 mg/day and a one-year study of once weekly FOSAMAX 70 mg) the rates of discontinuation of therapy due to any clinical adverse event were 2.7% for FOSAMAX 10 mg/day vs. 10.5% for placebo, and 6.4% for once weekly FOSAMAX 70 mg vs. 8.6% for placebo. The adverse reactions considered by the investigators as possibly, probably, or definitely drug related in greater than or equal to 2% of patients treated with either FOSAMAX or placebo are presented in Table 3.

Table 3: Osteoporosis Studies in Men Adverse Reactions Considered Possibly, Probably, or Definitely Drug Related by the Investigators and Reported in Greater Than or Equal to 2% of Patients
 | Two-year Study |  | One-year Study
 | FOSAMAX 10 mg/day % (n=146) | Placebo % (n=95) | Once Weekly FOSAMAX 70 mg % (n=109) | Placebo % (n=58)
Gastrointestinal acid regurgitation flatulence gastroesophageal reflux disease dyspepsia diarrhea abdominal pain nausea | 4.1 4.1 0.7 3.4 1.4 2.1 2.1 | 3.2 1.1 3.2 0.0 1.1 1.1 0.0 | 0.0 0.0 2.8 2.8 2.8 0.9 0.0 | 0.0 0.0 0.0 1.7 0.0 3.4 0.0

FOSAMAX PLUS D

In a fifteen-week double-blind, multinational study in osteoporotic postmenopausal women (n=682) and men (n=35), the safety profile of FOSAMAX PLUS D (70 mg/2800 international units) was similar to that of FOSAMAX once weekly 70 mg. In the 24-week double-blind extension study in women (n=619) and men (n=33), the safety profile of FOSAMAX PLUS D (70 mg/2800 international units) administered with an additional 2800 international units vitamin D3 was similar to that of FOSAMAX PLUS D (70 mg/2800 international units).

6.2 Post-Marketing Experience

The following adverse reactions have been identified during post-approval use of FOSAMAX, FOSAMAX PLUS D, or bisphosphonate products. Because these reactions are reported voluntarily from a population of uncertain size, it is not always possible to reliably estimate their frequency or establish a causal relationship to drug exposure.

Body as a Whole: hypersensitivity reactions including urticaria and angioedema. Transient symptoms of myalgia, malaise, asthenia and rarely, fever have been reported with alendronate, typically in association with initiation of treatment. Symptomatic hypocalcemia has occurred, generally in association with predisposing conditions. Peripheral edema.

Gastrointestinal: esophagitis, esophageal erosions, esophageal ulcers, esophageal stricture or perforation, and oropharyngeal ulceration. Gastric or duodenal ulcers, some severe and with complications have also been reported [see Dosage and Administration (2.3) and Warnings and Precautions (5.1)].

Localized osteonecrosis of the jaw, generally associated with tooth extraction and/or local infection with delayed healing, has been reported [see Warnings and Precautions (5.4)].

Musculoskeletal: bone, joint, and/or muscle pain, occasionally severe, and incapacitating [see Warnings and Precautions (5.3)]; joint swelling; low-energy femoral shaft and subtrochanteric fractures, and atypical fractures of other bones [see Warnings and Precautions (5.5)].

Nervous System: dizziness and vertigo.

Pulmonary: acute asthma exacerbations.

Skin: rash (occasionally with photosensitivity), pruritus, alopecia, severe skin reactions, including Stevens-Johnson syndrome and toxic epidermal necrolysis.

Special Senses: uveitis, scleritis or episcleritis. Cholesteatoma of the external auditory canal (focal osteonecrosis).

7 DRUG INTERACTIONS

7.1 Calcium Supplements/Antacids

Co-administration of FOSAMAX PLUS D and calcium, antacids, or oral medications containing multivalent cations will interfere with absorption of alendronate. Therefore, instruct patients to wait at least one-half hour after taking FOSAMAX PLUS D before taking any other oral medications.

7.2 Aspirin

In clinical studies, the incidence of upper gastrointestinal adverse events was increased in patients receiving concomitant therapy with daily doses of FOSAMAX greater than 10 mg and aspirin-containing products.

7.3 Nonsteroidal Anti-Inflammatory Drugs

FOSAMAX PLUS D may be administered to patients taking nonsteroidal anti-inflammatory drugs (NSAIDs). In a 3-year, controlled, clinical study (n=2027) during which a majority of patients received concomitant NSAIDs, the incidence of upper gastrointestinal adverse events was similar in patients taking FOSAMAX 5 or 10 mg/day compared to those taking placebo. However, since NSAID use is associated with gastrointestinal irritation, caution should be used during concomitant use with FOSAMAX PLUS D.

7.4 Drugs that May Impair the Absorption of Cholecalciferol

Olestra, mineral oils, orlistat, and bile acid sequestrants (e.g., cholestyramine, colestipol) may impair the absorption of vitamin D. Additional vitamin D supplementation should be considered [see Clinical Pharmacology (12.3)].

7.5 Drugs that May Increase the Catabolism of Cholecalciferol

Anticonvulsants, cimetidine, and thiazides may increase the catabolism of vitamin D. Additional vitamin D supplementation should be considered [see Clinical Pharmacology (12.3)].

8 USE IN SPECIFIC POPULATIONS

8.1 Pregnancy

Risk Summary

Available data on the use of FOSAMAX plus vitamin D use in pregnant women are insufficient to inform a drug-associated risk of adverse maternal or fetal outcomes. Discontinue FOSAMAX PLUS D when pregnancy is recognized.

Alendronate Sodium

In animal reproduction studies, daily oral administration of alendronate to rats from before mating through the end of gestation or lactation showed decreased postimplantation survival and decreased pup body weight gain starting at doses equivalent to less than half of the highest recommended 40 mg clinical daily dose (based on body surface area, mg/m^2). Oral administration of alendronate to rats during organogenesis resulted in reduced fetal ossification starting at doses 3 times the 40 mg clinical daily dose. No similar fetal effects were observed in pregnant rabbits dosed orally during organogenesis at doses equivalent to approximately 10 times the 40 mg clinical daily dose.

Delayed or failed delivery of offspring, protracted parturition, and late pregnancy maternal and fetal deaths due to maternal hypocalcemia occurred in rats at oral doses as low as one tenth the 40 mg clinical daily dose (see Data).

Bisphosphonates are incorporated into the bone matrix, from which they are gradually released over a period of years. The amount of bisphosphonate incorporated into adult bone and available for release into the systemic circulation is directly related to the dose and duration of bisphosphonate use. Consequently, based on the mechanism of action of bisphosphonates, there is a potential risk of fetal harm, predominantly skeletal, if a woman becomes pregnant after completing a course of bisphosphonate therapy. The impact of variables such as time between cessation of bisphosphonate therapy to conception, the particular bisphosphonate used, and the route of administration (intravenous versus oral) on the risk has not been studied.

Cholecalciferol

No data are available for cholecalciferol (vitamin D3) in animals. However, administration of high doses of vitamin D2 to pregnant rabbits resulted in abortions and an increased incidence of fetal aortic stenosis. Administration of high doses of vitamin D2 to pregnant rats resulted in neonatal death, decreased fetal weight, and impaired osteogenesis of long bones postnatally.

(See Data.)

The estimated background risk of major birth defects and miscarriage for the indicated population(s) is unknown. All pregnancies have a background risk of birth defects, loss, or other adverse outcomes. In the U.S. general population, the estimated background risks of major birth defects and miscarriage in clinically recognized pregnancies is 2-4% and 15-20%, respectively.

Data

Animal Data

Alendronate Sodium

Reproduction studies in rats dosed orally from before mating to the end of gestation or lactation showed decreased postimplantation survival starting at 2 mg/kg/day and decreased body weight gain starting at 1 mg/kg/day, doses equivalent to less than half the 40 mg clinical daily dose based on body surface area, mg/m^2. Incidence of incomplete fetal ossification in vertebral, skull, and sternebral bones were increased in rats dosed orally during organogenesis starting at 10 mg/kg/day (approximately 3 times the 40 mg clinical daily dose). No similar fetal effects were observed in pregnant rabbits dosed orally during organogenesis at up to 35 mg/kg/day (equivalent to approximately 10 times the 40 mg clinical daily dose).

Both total and ionized calcium decreased in pregnant rats dosed orally with 15 mg/kg/day alendronate (approximately 4 times the 40 mg clinical daily dose) resulting in delays and failures of delivery. Protracted parturition due to maternal hypocalcemia was observed when rats were treated from before mating through gestation starting at 0.5 mg/kg/day (approximately one tenth the 40 mg clinical daily dose). Maternotoxicity (late pregnancy deaths) also occurred in female rats treated orally with 15 mg/kg/day (approximately 4 times the 40 mg clinical daily dose) for varying gestational time periods. These maternal deaths were lessened but not eliminated by cessation of treatment. Calcium supplementation in the drinking water or by subcutaneous minipump to rats dosed orally with 15 mg/kg/day alendronate could not ameliorate the hypocalcemia or prevent the dystocia-related maternal and neonatal deaths. However, intravenous calcium supplementation prevented maternal, but not neonatal deaths.

Cholecalciferol

Administration of high doses (greater than or equal to 10,000 international units/every other day during pregnancy) of ergocalciferol (vitamin D2) to pregnant rabbits resulted in abortions and an increased incidence of fetal aortic stenosis. Administration of vitamin D2 (40,000 international units/day) to pregnant rats from gestation day 10 to 21 (organogenesis) resulted in neonatal death, decreased fetal weight, and impaired osteogenesis of long bones postnatally.

8.2 Lactation

Risk Summary

Cholecalciferol and some of its active metabolites pass into breast milk. It is not known whether alendronate is present in human breast milk, affects human milk production, or has effects on the breastfed infant. The developmental and health benefits of breastfeeding should be considered along with the mother's clinical need for FOSAMAX PLUS D and any potential adverse effects on the breastfed child from FOSAMAX PLUS D or from the underlying maternal condition.

8.4 Pediatric Use

FOSAMAX PLUS D is not indicated for use in pediatric patients.

The safety and efficacy of alendronate were examined in a randomized, double-blind, placebo-controlled two-year study of 139 pediatric patients, aged 4-18 years, with severe osteogenesis imperfecta (OI). One-hundred-and-nine patients were randomized to 5 mg alendronate daily (weight less than 40 kg) or 10 mg alendronate daily (weight greater than or equal to 40 kg) and 30 patients to placebo. The mean baseline lumbar spine BMD Z-score of the patients was -4.5. The mean change in lumbar spine BMD Z-score from baseline to Month 24 was 1.3 in the alendronate-treated patients and 0.1 in the placebo-treated patients. Treatment with alendronate did not reduce the risk of fracture. Sixteen percent of the alendronate patients who sustained a radiologically-confirmed fracture by Month 12 of the study had delayed fracture healing (callus remodeling) or fracture non-union when assessed radiographically at Month 24 compared with 9% of the placebo-treated patients. In alendronate-treated patients, bone histomorphometry data obtained at Month 24 demonstrated decreased bone turnover and delayed mineralization time; however, there were no mineralization defects. There were no statistically significant differences between the alendronate and placebo groups in reduction of bone pain. The oral bioavailability of alendronate in children was similar to that observed in adults.

8.5 Geriatric Use

Of the patients receiving FOSAMAX in the Fracture Intervention Trial (FIT), 71% (n=2302) were greater than or equal to 65 years of age and 17% (n=550) were greater than or equal to 75 years of age. Of the patients receiving FOSAMAX in the United States and Multinational osteoporosis treatment studies in women, and osteoporosis studies in men [see Clinical Studies (14.1, 14.2)], 45% and 54%, respectively, were 65 years of age or over. No overall differences in efficacy or safety were observed between these patients and younger patients, but greater sensitivity of some older individuals cannot be ruled out. Dietary requirements of vitamin D3 are increased in the elderly.

8.6 Renal Impairment

FOSAMAX PLUS D is not recommended for patients with creatinine clearance less than 35 mL/min. No dosage adjustment is necessary in patients with creatinine clearance values between 35-60 mL/min [see Clinical Pharmacology (12.3)].

8.7 Hepatic Impairment

Alendronate Sodium

As there is evidence that alendronate is not metabolized or excreted in the bile, no studies were conducted in patients with hepatic impairment. No dosage adjustment is necessary [see Clinical Pharmacology (12.3)].

Cholecalciferol

Vitamin D3 may not be adequately absorbed in patients who have malabsorption due to inadequate bile production.

10 OVERDOSAGE

Alendronate Sodium

Significant lethality after single oral doses with alendronate was seen in female rats and mice at 552 mg/kg (3256 mg/m^2) and 966 mg/kg (2898 mg/m^2), respectively. In males, these values were slightly higher, 626 and 1280 mg/kg, respectively. There was no lethality in dogs at oral doses up to 200 mg/kg (4000 mg/m^2).

No specific information is available on the treatment of overdosage with alendronate. Hypocalcemia, hypophosphatemia, and upper gastrointestinal adverse events, such as upset stomach, heartburn, esophagitis, gastritis, or ulcer, may result from oral overdosage. Milk or antacids should be given to bind alendronate. Due to the risk of esophageal irritation, vomiting should not be induced and the patient should remain fully upright.

Dialysis would not be beneficial.

Cholecalciferol

Significant lethality occurred in mice treated with a single high oral dose of calcitriol (4 mg/kg), the hormonal metabolite of cholecalciferol.

There is limited information regarding doses of cholecalciferol associated with acute toxicity, although intermittent (yearly or twice yearly) single doses of ergocalciferol (vitamin D2) as high as 600,000 international units have been given without reports of toxicity. Signs and symptoms of vitamin D toxicity include hypercalcemia, hypercalciuria, anorexia, nausea, vomiting, polyuria, polydipsia, weakness, and lethargy. Serum and urine calcium levels should be monitored in patients with suspected vitamin D toxicity. Standard therapy includes restriction of dietary calcium, hydration, and systemic glucocorticoids in patients with severe hypercalcemia.

Dialysis to remove vitamin D would not be beneficial.

11 DESCRIPTION

FOSAMAX PLUS D contains alendronate sodium, a bisphosphonate, and cholecalciferol (vitamin D3).

Alendronate sodium is a bisphosphonate that acts as a specific inhibitor of osteoclast-mediated bone resorption. Bisphosphonates are synthetic analogs of pyrophosphate that bind to the hydroxyapatite found in bone.

Alendronate sodium is chemically described as (4-amino-1-hydroxybutylidene) bisphosphonic acid monosodium salt trihydrate.

The empirical formula of alendronate sodium is C4H12NNaO7P2•3H2O and its formula weight is 325.12. The structural formula is:

Alendronate sodium is a white, crystalline, nonhygroscopic powder. It is soluble in water, very slightly soluble in alcohol, and practically insoluble in chloroform.

Cholecalciferol (vitamin D3) is a secosterol that is the natural precursor of the calcium-regulating hormone calcitriol (1,25 dihydroxyvitamin D3).

The chemical name of cholecalciferol is (3β,5Z,7E)-9,10-secocholesta-5,7,10(19)-trien-3-ol. The empirical formula of cholecalciferol is C27H44O and its molecular weight is 384.6. The structural formula is:

Cholecalciferol is a white, crystalline, odorless powder. Cholecalciferol is practically insoluble in water, freely soluble in usual organic solvents, and slightly soluble in vegetable oils.

FOSAMAX PLUS D for oral administration contains 91.37 mg of alendronate monosodium salt trihydrate, the molar equivalent of 70 mg of free acid, and 70 or 140 mcg of cholecalciferol, equivalent to 2800 or 5600 international units vitamin D, respectively. Each tablet contains the following inactive ingredients: microcrystalline cellulose, lactose anhydrous, medium chain triglycerides, gelatin, croscarmellose sodium, sucrose, colloidal silicon dioxide, magnesium stearate, butylated hydroxytoluene, modified food starch, and sodium aluminum silicate.

12 CLINICAL PHARMACOLOGY

12.1 Mechanism of Action

Alendronate Sodium

Animal studies have indicated the following mode of action. At the cellular level, alendronate shows preferential localization to sites of bone resorption, specifically under osteoclasts. The osteoclasts adhere normally to the bone surface but lack the ruffled border that is indicative of active resorption. Alendronate does not interfere with osteoclast recruitment or attachment, but it does inhibit osteoclast activity. Studies in mice on the localization of radioactive [^3H]alendronate in bone showed about 10-fold higher uptake on osteoclast surfaces than on osteoblast surfaces. Bones examined 6 and 49 days after [^3H]alendronate administration in rats and mice, respectively, showed that normal bone was formed on top of the alendronate, which was incorporated inside the matrix. While incorporated in bone matrix, alendronate is not pharmacologically active. Thus, alendronate must be continuously administered to suppress osteoclasts on newly formed resorption surfaces. Histomorphometry in baboons and rats showed that alendronate treatment reduces bone turnover (i.e., the number of sites at which bone is remodeled). In addition, bone formation exceeds bone resorption at these remodeling sites, leading to progressive gains in bone mass.

Cholecalciferol

Vitamin D3 is produced in the skin by photochemical conversion of 7-dehydrocholesterol to previtamin D3 by ultraviolet light. This is followed by non-enzymatic isomerization to vitamin D3. In the absence of adequate sunlight exposure, vitamin D3 is an essential dietary nutrient. Vitamin D3 in skin and dietary vitamin D3 (absorbed into chylomicrons) is converted to 25-hydroxyvitamin D3 in the liver. Conversion to the active calcium-mobilizing hormone 1,25-dihydroxyvitamin D3 (calcitriol) in the kidney is stimulated by both parathyroid hormone and hypophosphatemia. The principal action of 1,25-dihydroxyvitamin D3 is to increase intestinal absorption of both calcium and phosphate as well as regulate serum calcium, renal calcium and phosphate excretion, bone formation and bone resorption.

Vitamin D is required for normal bone formation. Vitamin D insufficiency develops when both sunlight exposure and dietary intake are inadequate. Insufficiency is associated with negative calcium balance, increased parathyroid hormone levels, bone loss, and increased risk of skeletal fracture. In severe cases, deficiency results in more severe hyperparathyroidism, hypophosphatemia, proximal muscle weakness, bone pain and osteomalacia.

12.2 Pharmacodynamics

Alendronate Sodium

Alendronate is a bisphosphonate that binds to bone hydroxyapatite and specifically inhibits the activity of osteoclasts, the bone-resorbing cells. Alendronate reduces bone resorption with no direct effect on bone formation, although the latter process is ultimately reduced because bone resorption and formation are coupled during bone turnover.

Daily oral doses of alendronate (5, 20, and 40 mg for six weeks) in postmenopausal women produced biochemical changes indicative of dose-dependent inhibition of bone resorption, including decreases in urinary calcium and urinary markers of bone collagen degradation (such as deoxypyridinoline and cross-linked N-telopeptides of type I collagen). These biochemical changes tended to return toward baseline values as early as 3 weeks following the discontinuation of therapy with alendronate and did not differ from placebo after 7 months.

Long-term treatment of osteoporosis with FOSAMAX 10 mg/day (for up to five years) reduced urinary excretion of markers of bone resorption, deoxypyridinoline and cross-linked N-telopeptides of type l collagen, by approximately 50% and 70%, respectively, to reach levels similar to those seen in healthy premenopausal women. The decrease in the rate of bone resorption indicated by these markers was evident as early as one month and at three to six months reached a plateau that was maintained for the entire duration of treatment with FOSAMAX. In osteoporosis treatment studies FOSAMAX 10 mg/day decreased the markers of bone formation, osteocalcin and bone specific alkaline phosphatase by approximately 50%, and total serum alkaline phosphatase by approximately 25 to 30% to reach a plateau after 6 to 12 months. Similar reductions in the rate of bone turnover were observed in postmenopausal women during one-year studies with once weekly FOSAMAX 70 mg for the treatment of osteoporosis. These data indicate that the rate of bone turnover reached a new steady-state, despite the progressive increase in the total amount of alendronate deposited within bone.

As a result of inhibition of bone resorption, asymptomatic reductions in serum calcium and phosphate concentrations were also observed following treatment with FOSAMAX. In the long-term studies, reductions from baseline in serum calcium (approximately 2%) and phosphate (approximately 4 to 6%) were evident the first month after the initiation of FOSAMAX 10 mg. No further decreases in serum calcium were observed for the five-year duration of treatment; however, serum phosphate returned toward prestudy levels during years three through five. In one-year studies with once weekly FOSAMAX 70 mg, similar reductions were observed at 6 and 12 months. The reduction in serum phosphate may reflect not only the positive bone mineral balance due to FOSAMAX but also a decrease in renal phosphate reabsorption.

Osteoporosis in Men

Treatment of men with osteoporosis with FOSAMAX 10 mg/day for two years reduced urinary excretion of cross-linked N-telopeptides of type I collagen by approximately 60% and bone-specific alkaline phosphatase by approximately 40%. Similar reductions were observed in a one-year study in men with osteoporosis receiving once weekly FOSAMAX 70 mg.

Cholecalciferol

Vitamin D is required for normal bone formation. Vitamin D insufficiency is associated with negative calcium balance, leading to increased parathyroid hormone levels and worsening of bone loss associated with osteoporosis. When taken without vitamin D, alendronate is also associated with a reduction in serum calcium concentrations and increased parathyroid hormone levels. In a 15-week trial, 717 postmenopausal women and men, mean age 67 years, with osteoporosis (lumbar spine bone mineral density [BMD] of at least 2.5 standard deviations below the premenopausal mean) were randomized to receive either weekly FOSAMAX PLUS D 70 mg/2800 international units vitamin D or weekly FOSAMAX 70 mg alone with no vitamin D supplementation. Patients who were vitamin D deficient (25-hydroxyvitamin D less than 9 ng/mL) at baseline were excluded. Treatment with FOSAMAX PLUS D 70 mg/2800 international units resulted in a smaller reduction in serum calcium levels (-0.9%) when compared to FOSAMAX 70 mg alone (-1.4%). As well, treatment with FOSAMAX PLUS D 70 mg/2800 international units resulted in a significantly smaller increase in parathyroid hormone levels when compared to FOSAMAX 70 mg alone (14% and 24%, respectively).

The sufficiency of patients' vitamin D status is best assessed by measuring 25-hydroxyvitamin D levels. In the 15-week trial mentioned above, baseline 25-hydroxyvitamin D levels were 22.2 ng/mL in the FOSAMAX PLUS D group and 22.1 ng/mL in the FOSAMAX only group. After 15 weeks of treatment, the mean levels were 23.1 ng/mL and 18.4 ng/mL in the FOSAMAX PLUS D and FOSAMAX only groups, respectively. The final levels of 25-hydroxyvitamin D at Week 15 are summarized in Table 4.

Table 4: 25-hydroxyvitamin D Levels after Treatment with FOSAMAX PLUS D (70 mg/2800 international units) or FOSAMAX 70 mg at Week 15 [Patients who were vitamin D deficient (25-hydroxyvitamin D less than 9 ng/mL) at baseline were excluded.]
 | Number (%) of Patients
25-hydroxyvitamin D Ranges (ng/mL) | <9 | 9-14 | 15-19 | 20-24 | 25-29 | 30-62
FOSAMAX PLUS D (70 mg/2800 international units) (N=357) | 4 (1.1) | 37 (10.4) | 87 (24.4) | 84 (23.5) | 82 (23.0) | 63 (17.7)
FOSAMAX 70 mg (N=351) | 46 (13.1) | 66 (18.8) | 108 (30.8) | 58 (16.5) | 37 (10.5) | 36 (10.3)

Patients (n=652) who completed the above 15-week trial continued in a 24-week extension in which all received FOSAMAX PLUS D (70 mg/2800 international units) and were randomly assigned to receive either additional once weekly vitamin D3 2800 international units (Vitamin D3 5600 international units group) or matching placebo (Vitamin D3 2800 international units group). After 24 weeks of extended treatment (Week 39 from original baseline), the mean levels of 25-hydroxyvitamin D were 27.9 ng/mL and 25.6 ng/mL in the vitamin D3 5600 international units group and vitamin D3 2800 international units group, respectively. The percentage of patients with hypercalciuria at Week 39 was not statistically different between treatment groups.

The distribution of the final levels of 25-hydroxyvitamin D at Week 39 is summarized in Table 5.

Table 5: 25-hydroxyvitamin D Levels after Treatment with FOSAMAX PLUS D at Week 39
 | Number (%) of Patients
25-hydroxyvitamin D Ranges (ng/mL) | <9 | 9-14 | 15-19 | 20-24 | 25-29 | 30-59
FOSAMAX PLUS D (Vitamin D3 5600 international units group) [Patients received FOSAMAX 70 mg or FOSAMAX PLUS D (70 mg/2800 international units) for the 15-week base study followed by FOSAMAX PLUS D (70 mg/2800 international units) and 2800 international units additional vitamin D3 for the 24-week extension study.] (N=321) | 0 | 10 (3.1) | 29 (9.0) | 79 (24.6) | 87 (27.1) | 116 (36.1)
FOSAMAX PLUS D (Vitamin D3 2800 international units group) [Patients received FOSAMAX 70 mg or FOSAMAX PLUS D (70 mg/2800 international units) for 15-week base study followed by FOSAMAX PLUS D (70 mg/2800 international units) and placebo for the additional vitamin D3 for 24-week extension study.] (N=320) | 1 (0.3) | 17 (5.3) | 56 (17.5) | 80 (25.0) | 74 (23.1) | 92 (28.8)

12.3 Pharmacokinetics

Absorption

Alendronate Sodium

Relative to an intravenous reference dose, the mean oral bioavailability of alendronate in women was 0.64% for doses ranging from 5 to 70 mg when administered after an overnight fast and two hours before a standardized breakfast. Oral bioavailability of the 10-mg tablet in men (0.59%) was similar to that in women when administered after an overnight fast and 2 hours before breakfast.

In a study, the alendronate in the FOSAMAX PLUS D (70 mg/2800 international units) tablet and the FOSAMAX (alendronate sodium) 70-mg tablet were found to be equally bioavailable. In a separate study, the alendronate in the FOSAMAX PLUS D (70 mg/5600 international units) tablet was found to be equally bioavailable to the alendronate in the FOSAMAX (alendronate sodium) 70-mg tablet.

A study examining the effect of timing of a meal on the bioavailability of alendronate was performed in 49 postmenopausal women. Bioavailability was decreased (by approximately 40%) when 10 mg alendronate was administered either 0.5 or 1 hour before a standardized breakfast, when compared to dosing 2 hours before eating. In studies of treatment and prevention of osteoporosis, alendronate was effective when administered at least 30 minutes before breakfast.

Bioavailability was negligible whether alendronate was administered with or up to two hours after a standardized breakfast. Concomitant administration of alendronate with coffee or orange juice reduced bioavailability by approximately 60%.

Cholecalciferol

Following administration of FOSAMAX PLUS D (70 mg/2800 international units) after an overnight fast and two hours before a standard meal, the baseline adjusted mean area under the serum-concentration-time curve (AUC0-120 hrs) for vitamin D3 was 120.7 ng-hr/mL. The baseline adjusted mean maximal serum concentration (Cmax) of vitamin D3 was 4.0 ng/mL, and the baseline adjusted mean time to maximal serum concentration (Tmax) was 10.6 hrs. The bioavailability of the 2800 international units vitamin D3 in FOSAMAX PLUS D is similar to 2800 international units vitamin D3 administered alone.

In a separate study, the baseline adjusted mean AUC0-80 hrs and baseline adjusted mean Cmax for vitamin D3 were 355.6 ng-hr/mL and 10.8 ng/mL, respectively. The baseline adjusted mean Tmax was 9.2 hrs. The bioavailability of the 5600 international units vitamin D3 in the FOSAMAX PLUS D is similar to 5600 international units vitamin D3 administered as two 2800 international units vitamin D3 tablets.

Distribution

Alendronate Sodium

Preclinical studies (in male rats) show that alendronate transiently distributes to soft tissues following 1 mg/kg intravenous administration but is then rapidly redistributed to bone or excreted in the urine. The mean steady-state volume of distribution, exclusive of bone, is at least 28 L in humans. Concentrations of drug in plasma following therapeutic oral doses are too low (less than 5 ng/mL) for analytical detection. Protein binding in human plasma is approximately 78%.

Cholecalciferol

Following absorption, vitamin D3 enters the blood as part of chylomicrons. Vitamin D3 is rapidly distributed mostly to the liver where it undergoes metabolism to 25-hydroxyvitamin D3, the major storage form. Lesser amounts are distributed to adipose tissue and stored as vitamin D3 at these sites for later release into the circulation. Circulating vitamin D3 is bound to vitamin D-binding protein.

Metabolism

Alendronate Sodium

There is no evidence that alendronate is metabolized in animals or humans.

Cholecalciferol

Vitamin D3 is rapidly metabolized by hydroxylation in the liver to 25-hydroxyvitamin D3, and subsequently metabolized in the kidney to 1,25-dihydroxyvitamin D3, which represents the biologically active form. Further hydroxylation occurs prior to elimination. A small percentage of vitamin D3 undergoes glucuronidation prior to elimination.

Excretion

Alendronate Sodium

Following a single intravenous dose of [^14C]alendronate, approximately 50% of the radioactivity was excreted in the urine within 72 hours and little or no radioactivity was recovered in the feces. Following a single 10-mg intravenous dose, the renal clearance of alendronate was 71 mL/min (64, 78; 90% confidence interval [CI]), and systemic clearance did not exceed 200 mL/min. Plasma concentrations fell by more than 95% within 6 hours following intravenous administration. The terminal half-life in humans is estimated to exceed 10 years, probably reflecting release of alendronate from the skeleton. Based on the above, it is estimated that after 10 years of oral treatment with FOSAMAX (10 mg daily) the amount of alendronate released daily from the skeleton is approximately 25% of that absorbed from the gastrointestinal tract.

Cholecalciferol

When radioactive vitamin D3 was intravenously administered to healthy subjects, the mean urinary excretion of radioactivity after 48 hours was 2.4% of the administered dose, and the mean fecal excretion of radioactivity after 48 hours was 4.9% of the administered dose. In both cases, the excreted radioactivity was almost exclusively as metabolites of the parent. The mean half-life of baseline adjusted vitamin D3 in the serum following an oral dose of FOSAMAX PLUS D is approximately 14 hours.

Specific Populations

Gender: Bioavailability and the fraction of an intravenous dose of alendronate excreted in urine were similar in men and women.

Geriatric:

Alendronate Sodium

Bioavailability and disposition of alendronate (urinary excretion) were similar in elderly and younger patients. No dosage adjustment of alendronate is necessary.

Cholecalciferol

Dietary requirements of vitamin D3 are increased in the elderly.

Race: Pharmacokinetic differences due to race have not been studied.

Renal Impairment:

Alendronate Sodium

Preclinical studies show that, in rats with kidney failure, increasing amounts of drug are present in plasma, kidney, spleen, and tibia. In healthy controls, drug that is not deposited in bone is rapidly excreted in the urine. No evidence of saturation of bone uptake was found after 3 weeks dosing with cumulative intravenous doses of 35 mg/kg in young male rats. Although no formal renal impairment pharmacokinetic study has been conducted in patients, it is likely that, as in animals, elimination of alendronate via the kidney will be reduced in patients with impaired renal function. Therefore, somewhat greater accumulation of alendronate in bone might be expected in patients with impaired renal function.

No dosage adjustment is necessary for patients with creatinine clearance 35 to 60 mL/min. FOSAMAX PLUS D is not recommended for patients with creatinine clearance less than 35 mL/min due to lack of experience with alendronate in renal failure.

Cholecalciferol

Patients with renal insufficiency will have decreased ability to form the active 1,25-dihydroxyvitamin D3 metabolite.

Hepatic Impairment:

Alendronate Sodium

As there is evidence that alendronate is not metabolized or excreted in the bile, no studies were conducted in patients with hepatic impairment. No dosage adjustment is necessary.

Cholecalciferol

Vitamin D3 may not be adequately absorbed in patients who have malabsorption due to inadequate bile production.

Drug Interactions

Alendronate Sodium

Intravenous ranitidine was shown to double the bioavailability of oral alendronate. The clinical significance of this increased bioavailability and whether similar increases will occur in patients given oral H2-antagonists is unknown.

In healthy subjects, oral prednisone (20 mg three times daily for five days) did not produce a clinically meaningful change in the oral bioavailability of alendronate (a mean increase ranging from 20 to 44%).

Products containing calcium and other multivalent cations are likely to interfere with absorption of alendronate.

Cholecalciferol

Olestra, mineral oils, orlistat, and bile acid sequestrants (e.g., cholestyramine, colestipol) may impair the absorption of vitamin D. Anticonvulsants, cimetidine, and thiazides may increase the catabolism of vitamin D.

13 NONCLINICAL TOXICOLOGY

13.1 Carcinogenesis, Mutagenesis, Impairment of Fertility

The following data are based on findings for the individual components of FOSAMAX PLUS D.

Alendronate Sodium

Harderian gland (a retro-orbital gland not present in humans) adenomas were increased in high-dose female mice (p=0.003) in a 92-week oral carcinogenicity study at doses of alendronate of 1, 3, and 10 mg/kg/day (males) or 1, 2, and 5 mg/kg/day (females). These doses are equivalent to 0.5 to 4 times the highest recommended clinical daily dose of 10 mg based on surface area, mg/m^2. The relevance of this finding to humans is unknown.

Parafollicular cell (thyroid) adenomas were increased in high-dose male rats (p=0.003) in a 2-year oral carcinogenicity study at doses of 1 and 3.75 mg/kg body weight. These doses are equivalent to 1 and 4 times the 10-mg clinical daily dose based on surface area, mg/m^2. The relevance of this finding to humans is unknown.

Alendronate was not genotoxic in the in vitro microbial mutagenesis assay with and without metabolic activation, in an in vitro mammalian cell mutagenesis assay, in an in vitro alkaline elution assay in rat hepatocytes, and in an in vivo chromosomal aberration assay in mice. In an in vitro chromosomal aberration assay in Chinese hamster ovary cells, however, alendronate gave equivocal results.

Alendronate had no effect on fertility (male or female) in rats at oral doses up to 5 mg/kg/day (4 times the 10-mg clinical daily dose based on surface area, mg/m^2).

Cholecalciferol

The carcinogenic potential of cholecalciferol (vitamin D3) has not been studied in rodents. Calcitriol, the hormonal metabolite of cholecalciferol, was not genotoxic in the Ames microbial mutagenesis assay with or without metabolic activation, and in an in vivo micronucleus assay in mice.

Ergocalciferol (vitamin D2) at high doses (150,000 to 200,000 international units/kg/day) administered prior to mating resulted in altered estrous cycle and inhibition of pregnancy in rats. The potential effect of cholecalciferol on male fertility is unknown in rats.

13.2 Animal Toxicology and/or Pharmacology

The relative inhibitory activities on bone resorption and mineralization of alendronate and etidronate were compared in the Schenk assay, which is based on histological examination of the epiphyses of growing rats. In this assay, the lowest dose of alendronate that interfered with bone mineralization (leading to osteomalacia) was 6000-fold the antiresorptive dose. The corresponding ratio for etidronate was one to one. These data suggest that alendronate administered in therapeutic doses is highly unlikely to induce osteomalacia.

14 CLINICAL STUDIES

14.1 Treatment of Osteoporosis in Postmenopausal Women

FOSAMAX Daily

The efficacy of FOSAMAX 10 mg daily was assessed in four clinical trials. Study 1, a three-year, multicenter, double-blind, placebo-controlled, US clinical study enrolled 478 patients with a BMD T-score at or below minus 2.5 with or without a prior vertebral fracture; Study 2, a three-year, multicenter, double-blind, placebo-controlled, Multinational clinical study enrolled 516 patients with a BMD T-score at or below minus 2.5 with or without a prior vertebral fracture; Study 3, the Three-Year Study of the Fracture Intervention Trial (FIT), a study which enrolled 2027 postmenopausal patients with at least one baseline vertebral fracture; and Study 4, the Four-Year Study of FIT, a study which enrolled 4432 postmenopausal patients with low bone mass but without a baseline vertebral fracture.

Effect on Fracture Incidence

To assess the effects of FOSAMAX on the incidence of vertebral fractures (detected by digitized radiography; approximately one third of these were clinically symptomatic), the U.S. and Multinational studies were combined in an analysis that compared placebo to the pooled dosage groups of FOSAMAX (5 or 10 mg for three years or 20 mg for two years followed by 5 mg for one year). There was a statistically significant reduction in the proportion of patients treated with FOSAMAX experiencing one or more new vertebral fractures relative to those treated with placebo (3.2% vs. 6.2%; a 48% relative risk reduction). A reduction in the total number of new vertebral fractures (4.2 vs. 11.3 per 100 patients) was also observed. In the pooled analysis, patients who received FOSAMAX had a loss in stature that was statistically significantly less than was observed in those who received placebo (-3.0 mm vs. -4.6 mm).

The Fracture Intervention Trial (FIT) consisted of two studies in postmenopausal women: the Three-Year Study of patients who had at least one baseline radiographic vertebral fracture and the Four-Year Study of patients with low bone mass but without a baseline vertebral fracture. In both studies of FIT, 96% of randomized patients completed the studies (i.e., had a closeout visit at the scheduled end of the study); approximately 80% of patients were still taking study medication upon completion.

Fracture Intervention Trial: Three-Year Study (patients with at least one baseline radiographic vertebral fracture)

This randomized, double-blind, placebo-controlled, 2027-patient study (FOSAMAX, n=1022; placebo, n=1005) demonstrated that treatment with FOSAMAX resulted in statistically significant reductions in fracture incidence at three years as shown in Table 6.

Table 6: Effect of FOSAMAX on Fracture Incidence in the Three-Year Study of FIT (patients with vertebral fracture at baseline)
 | Percent of Patients
 | FOSAMAX (n=1022) | Placebo (n=1005) | Absolute Reduction in Fracture Incidence | Relative Reduction in Fracture Risk %
Patients with:
Vertebral fractures (diagnosed by X-ray) [Number evaluable for vertebral fractures: FOSAMAX, n=984; placebo, n=966]
≥1 new vertebral fracture | 7.9 | 15.0 | 7.1 | 47 [p<0.001]
≥2 new vertebral fractures | 0.5 | 4.9 | 4.4 | 90
Clinical (symptomatic) fractures
Any clinical (symptomatic) fracture | 13.8 | 18.1 | 4.3 | 26 [p=0.007]
≥1 clinical (symptomatic) vertebral fracture | 2.3 | 5.0 | 2.7 | 54 [p<0.01]
Hip fracture | 1.1 | 2.2 | 1.1 | 51 [p<0.05]
Wrist (forearm) fracture | 2.2 | 4.1 | 1.9 | 48

Furthermore, in this population of patients with baseline vertebral fracture, treatment with FOSAMAX significantly reduced the incidence of hospitalizations (25.0% vs. 30.7%).

In the Three-Year Study of FIT, fractures of the hip occurred in 22 (2.2%) of 1005 patients on placebo and 11 (1.1%) of 1022 patients on FOSAMAX, p=0.047. Figure 1 displays the cumulative incidence of hip fractures in this study.

Figure 1:

Cumulative Incidence of Hip Fractures in the Three-Year Study of FIT
(patients with radiographic vertebral fracture at baseline)

Fracture Intervention Trial: Four-Year Study (patients with low bone mass but without a baseline radiographic vertebral fracture)

This randomized, double-blind, placebo-controlled, 4432-patient study (FOSAMAX, n=2214; placebo, n=2218) further investigated the reduction in fracture incidence due to FOSAMAX. The intent of the study was to recruit women with osteoporosis, defined as a baseline femoral neck BMD at least two standard deviations below the mean for young adult women. However, due to subsequent revisions to the normative values for femoral neck BMD, 31% of patients were found not to meet this entry criterion and thus this study included both osteoporotic and non-osteoporotic women. The results are shown in Table 7 below for the patients with osteoporosis.

Table 7: Effect of FOSAMAX on Fracture Incidence in Osteoporotic [Baseline femoral neck BMD at least 2 SD below the mean for young adult women] Patients in the Four-Year Study of FIT (patients without vertebral fracture at baseline)
 | Percent of Patients
 | FOSAMAX (n=1545) | Placebo (n=1521) | Absolute Reduction in Fracture Incidence | Relative Reduction in Fracture Risk (%)
Patients with:
Vertebral fractures (diagnosed by X-ray) [Number evaluable for vertebral fractures: FOSAMAX, n=1426; placebo, n=1428]
≥1 new vertebral fracture | 2.5 | 4.8 | 2.3 | 48 [p<0.001]
≥2 new vertebral fractures | 0.1 | 0.6 | 0.5 | 78 [p=0.035]
Clinical (symptomatic) fractures
Any clinical (symptomatic) fracture | 12.9 | 16.2 | 3.3 | 22 [p=0.01]
≥1 clinical (symptomatic) vertebral fracture | 1.0 | 1.6 | 0.6 | 41 (NS) [Not significant. This study was not powered to detect differences at these sites.]
Hip fracture | 1.0 | 1.4 | 0.4 | 29 (NS)
Wrist (forearm) fracture | 3.9 | 3.8 | -0.1 | NS

Fracture Results Across Studies

In the Three-Year Study of FIT, FOSAMAX reduced the percentage of women experiencing at least one new radiographic vertebral fracture from 15.0% to 7.9% (47% relative risk reduction, p<0.001); in the Four-Year Study of FIT, the percentage was reduced from 3.8% to 2.1% (44% relative risk reduction, p=0.001); and in the combined U.S./Multinational studies, from 6.2% to 3.2% (48% relative risk reduction, p=0.034).

FOSAMAX reduced the percentage of women experiencing multiple (two or more) new vertebral fractures from 4.2% to 0.6% (87% relative risk reduction, p<0.001) in the combined U.S./Multinational studies and from 4.9% to 0.5% (90% relative risk reduction, p<0.001) in the Three-Year Study of FIT. In the Four-Year Study of FIT, FOSAMAX reduced the percentage of osteoporotic women experiencing multiple vertebral fractures from 0.6% to 0.1% (78% relative risk reduction, p=0.035).

Thus, FOSAMAX reduced the incidence of radiographic vertebral fractures in osteoporotic women whether or not they had a previous radiographic vertebral fracture.

Effect on Bone Mineral Density

The bone mineral density efficacy of FOSAMAX 10 mg once daily in postmenopausal women, 44 to 84 years of age, with osteoporosis (lumbar spine bone mineral density [BMD] of at least 2 standard deviations below the premenopausal mean) was demonstrated in four double-blind, placebo-controlled clinical studies of two or three years' duration.

Figure 2 shows the mean increases in BMD of the lumbar spine, femoral neck, and trochanter in patients receiving FOSAMAX 10 mg/day relative to placebo-treated patients at three years for each of these studies.

Figure 2:

At three years significant increases in BMD, relative both to baseline and placebo, were seen at each measurement site in each study in patients who received FOSAMAX 10 mg/day. Total body BMD also increased significantly in each study, suggesting that the increases in bone mass of the spine and hip did not occur at the expense of other skeletal sites. Increases in BMD were evident as early as three months and continued throughout the three years of treatment. (See figure 3 for lumbar spine results.) In the two-year extension of these studies, treatment of 147 patients with FOSAMAX 10 mg/day resulted in continued increases in BMD at the lumbar spine and trochanter (absolute additional increases between years 3 and 5: lumbar spine, 0.94%; trochanter, 0.88%). BMD at the femoral neck, forearm and total body were maintained. FOSAMAX was similarly effective regardless of age, race, baseline rate of bone turnover, and baseline BMD in the range studied (at least 2 standard deviations below the premenopausal mean).

Figure 3:

In patients with postmenopausal osteoporosis treated with FOSAMAX 10 mg/day for one or two years, the effects of treatment withdrawal were assessed. Following discontinuation, there were no further increases in bone mass and the rates of bone loss were similar to those of the placebo groups.

Bone Histology

Bone histology in 270 postmenopausal patients with osteoporosis treated with FOSAMAX at doses ranging from 1 to 20 mg/day for one, two, or three years revealed normal mineralization and structure, as well as the expected decrease in bone turnover relative to placebo. These data, together with the normal bone histology and increased bone strength observed in rats and baboons exposed to long-term alendronate treatment, support the conclusion that bone formed during therapy with FOSAMAX is of normal quality.

Effect on Height

FOSAMAX, over a three- or four-year period, was associated with statistically significant reductions in loss of height vs. placebo in patients with and without baseline radiographic vertebral fractures. At the end of the FIT studies, the between-treatment group differences were 3.2 mm in the Three-Year Study and 1.3 mm in the Four-Year Study.

FOSAMAX Once-Weekly

The therapeutic equivalence of once-weekly FOSAMAX 70 mg (n=519) and FOSAMAX 10 mg daily (n=370) was demonstrated in a one-year, double-blind, multicenter study of postmenopausal women with osteoporosis. In the primary analysis of completers, the mean increases from baseline in lumbar spine BMD at one year were 5.1% (4.8, 5.4%; 95% CI) in the 70-mg once-weekly group (n=440) and 5.4% (5.0, 5.8%; 95% CI) in the 10-mg daily group (n=330). The two treatment groups were also similar with regard to BMD increases at other skeletal sites. The results of the intention-to-treat analysis were consistent with the primary analysis of completers.

Concomitant Use with Estrogen Hormone Replacement Therapy

The effects on BMD of treatment with FOSAMAX 10 mg once daily and conjugated estrogen (0.625 mg/day) either alone or in combination were assessed in a two-year, double-blind, placebo-controlled study of hysterectomized postmenopausal osteoporotic women (n=425). At two years, the increases in lumbar spine BMD from baseline were significantly greater with the combination (8.3%) than with either estrogen or FOSAMAX alone (both 6.0%).

The effects on BMD when FOSAMAX was added to stable doses (for at least one year) of HRT (estrogen ± progestin) were assessed in a one-year, double-blind, placebo-controlled study in postmenopausal osteoporotic women (n=428). The addition of FOSAMAX 10 mg once daily to HRT produced, at one year, significantly greater increases in lumbar spine BMD (3.7%) vs. HRT alone (1.1%).

In these studies, significant increases or favorable trends in BMD for combined therapy compared with HRT alone were seen at the total hip, femoral neck, and trochanter. No significant effect was seen for total body BMD.

Histomorphometric studies of transiliac biopsies in 92 subjects showed normal bone architecture. Compared to placebo there was a 98% suppression of bone turnover (as assessed by mineralizing surface) after 18 months of combined treatment with FOSAMAX and HRT, 94% on FOSAMAX alone, and 78% on HRT alone. The long-term effects of combined FOSAMAX and HRT on fracture occurrence and fracture healing have not been studied.

14.2 Treatment to Increase Bone Mass in Men with Osteoporosis

The efficacy of FOSAMAX in men with hypogonadal or idiopathic osteoporosis was demonstrated in two clinical studies.

FOSAMAX Daily

A two-year, double-blind, placebo-controlled, multicenter study of FOSAMAX 10 mg once daily enrolled a total of 241 men between the ages of 31 and 87 (mean, 63). All patients in the trial had either a BMD T-score less than or equal to -2 at the femoral neck and less than or equal to -1 at the lumbar spine, or a baseline osteoporotic fracture and a BMD T-score less than or equal to -1 at the femoral neck. At two years, the mean increases relative to placebo in BMD in men receiving FOSAMAX 10 mg/day were significant at the following sites: lumbar spine, 5.3%; femoral neck, 2.6%; trochanter, 3.1%; and total body, 1.6%. Treatment with FOSAMAX also reduced height loss (FOSAMAX, -0.6 mm vs. placebo, -2.4 mm).

FOSAMAX Once-Weekly

A one-year, double-blind, placebo-controlled, multicenter study of once weekly FOSAMAX 70 mg enrolled a total of 167 men between the ages of 38 and 91 (mean, 66). Patients in the study had either a BMD T-score less than or equal to -2 at the femoral neck and less than or equal to -1 at the lumbar spine, or a BMD T-score less than or equal to -2 at the lumbar spine and less than or equal to -1 at the femoral neck, or a baseline osteoporotic fracture and a BMD T-score less than or equal to -1 at the femoral neck. At one year, the mean increases relative to placebo in BMD in men receiving FOSAMAX 70 mg once weekly were significant at the following sites: lumbar spine, 2.8%; femoral neck, 1.9%; trochanter, 2.0%; and total body, 1.2%. These increases in BMD were similar to those seen at one year in the 10 mg once-daily study.

In both studies, BMD responses were similar regardless of age (greater than or equal to 65 years vs. less than 65 years), gonadal function (baseline testosterone less than 9 ng/dL vs. greater than or equal to 9 ng/dL), or baseline BMD (femoral neck and lumbar spine T-score less than or equal to -2.5 vs. greater than -2.5).

16 HOW SUPPLIED/STORAGE AND HANDLING

FOSAMAX PLUS D 70 mg/2800 international units are white to off-white, modified capsule-shaped tablets with code 710 on one side and an outline of a bone image on the other. They are supplied as follows:

NDC 78206-137-01 unit of use blister packages of 4.

FOSAMAX PLUS D 70 mg/5600 international units are white to off-white, modified rectangle-shaped tablets with code 270 on one side and an outline of a bone image on the other. They are supplied as follows:

NDC 78206-136-01 unit of use blister packages of 4

Storage

Store at 68°F to 77°F (20°C to 25°C), excursions between 59°F to 86°F (15°C to 30°C). are allowed. [See USP Controlled Room Temperature.] Protect from moisture and light. Store tablets in the original blister package until use.

17 PATIENT COUNSELING INFORMATION

Advise the patient to read the FDA-approved patient labeling (Medication Guide).

Instruct patients to read the Medication Guide before starting therapy with FOSAMAX PLUS D and to reread it each time the prescription is renewed.

Osteoporosis Recommendations, Including Calcium and Vitamin D Supplementation

Instruct patients to take supplemental calcium if intake is inadequate. Patients at increased risk for vitamin D insufficiency (e.g., over the age of 70 years, nursing home bound, or chronically ill) should take additional vitamin D if needed [see Dosage and Administration (2.4)]. Patients with gastrointestinal malabsorption syndromes may require additional vitamin D supplementation. Weight-bearing exercise should be considered along with the modification of certain behavioral factors, such as cigarette smoking and/or excessive alcohol consumption, if these factors exist.

Dosing Instructions

Instruct patients that the expected benefits of FOSAMAX PLUS D may only be obtained when it is taken with plain water the first thing upon arising for the day at least 30 minutes before the first food, beverage, or medication of the day. Even dosing with orange juice or coffee has been shown to markedly reduce the absorption of alendronate [see Clinical Pharmacology (12.3)].

Instruct patients not to chew or suck on the tablet because of a potential for oropharyngeal ulceration.

Instruct patients to swallow each tablet of FOSAMAX PLUS D with a full glass of water (6-8 ounces) and not to lie down for at least 30 minutes and until after their first food of the day to facilitate delivery to the stomach and thus reduce the potential for esophageal irritation.

Instruct patients not to take FOSAMAX PLUS D at bedtime or before arising for the day. Patients should be informed that failure to follow these instructions may increase their risk of esophageal problems.

Instruct patients that if they develop symptoms of esophageal disease (such as difficulty or pain upon swallowing, retrosternal pain or new or worsening heartburn) they should stop taking FOSAMAX PLUS D and consult their physician.

If patients miss a dose of FOSAMAX PLUS D, instruct patients to take one tablet on the morning after they remember. They should not take two tablets on the same day but should return to taking one tablet once a week, as originally scheduled on their chosen day.

Dist. by: Organon LLC, a subsidiary of
ORGANON & Co.,
Jersey City, NJ 07302, USA

For patent information: www.organon.com/our-solutions/patent/

© 2026 Organon group of companies. All rights reserved.

uspi-og0217a-t-2602r002

MEDICATION GUIDE
FOSAMAX® PLUS D (FOSS-ah-max PLUS D)
(alendronate sodium/cholecalciferol)
Tablets

Read the Medication Guide that comes with FOSAMAX® PLUS D before you start taking it and each time you get a refill. There may be new information. This Medication Guide does not take the place of talking with your doctor about your medical condition or treatment. Talk to your doctor if you have any questions about FOSAMAX PLUS D.

What is the most important information I should know about FOSAMAX PLUS D?

FOSAMAX PLUS D can cause serious side effects including:

1. Esophagus problems
2. Low calcium levels in your blood (hypocalcemia)
3. Bone, joint, or muscle pain
4. Severe jaw bone problems (osteonecrosis)
5. Unusual breaks in thigh and other bones

1. Esophagus problems.
  Some people who take FOSAMAX PLUS D may develop problems in the esophagus (the tube that connects the mouth and the stomach). These problems include irritation, inflammation, or ulcers of the esophagus which may sometimes bleed.
  - It is important that you take FOSAMAX PLUS D exactly as prescribed to help lower your chance of getting esophagus problems. (See the section "How should I take FOSAMAX PLUS D tablet?")
  - Stop taking FOSAMAX PLUS D and call your doctor right away if you get chest pain, new or worsening heartburn, or have trouble or pain when you swallow.
2. Low calcium levels in your blood (hypocalcemia).
  FOSAMAX PLUS D may lower the calcium levels in your blood. If you have low blood calcium before you start taking FOSAMAX PLUS D, it may get worse during treatment. Your low blood calcium must be treated before you take FOSAMAX PLUS D. Most people with low blood calcium levels do not have symptoms, but some people may have symptoms. Call your doctor right away if you have symptoms of low blood calcium such as:
  - Spasms, twitches, or cramps in your muscles
  - Numbness or tingling in your fingers, toes, or around your mouth
  Your doctor may prescribe calcium and vitamin D to help prevent low calcium levels in your blood, while you take FOSAMAX PLUS D. Take calcium and vitamin D as your doctor tells you to.
3. Bone, joint, or muscle pain.
  Some people who take FOSAMAX PLUS D develop severe bone, joint, or muscle pain.
4. Severe jaw bone problems (osteonecrosis).
  Severe jaw bone problems may happen when you take FOSAMAX PLUS D. Your doctor should examine your mouth before you start FOSAMAX PLUS D. Your doctor may tell you to see your dentist before you start FOSAMAX PLUS D. It is important for you to practice good mouth care during treatment with FOSAMAX PLUS D.
5. Unusual breaks in thigh and other bones.
  Some people have had unusual bone breaks, including thigh bone when taking FOSAMAX PLUS D. A break in the thigh bone can feel like a new pain in your hip, groin, or thigh. People taking FOSAMAX PLUS D can also have breaks in other bones.

Call your doctor right away if you have any of these side effects.

What is FOSAMAX PLUS D?

FOSAMAX PLUS D is a prescription medicine used to:

- Treat osteoporosis in women after menopause. FOSAMAX PLUS D helps increase bone mass and reduces the chance of having a hip or spinal fracture (break).
- Increase bone mass in men with osteoporosis.

FOSAMAX PLUS D should not be used to treat vitamin D deficiency.

It is not known how long FOSAMAX PLUS D works for the treatment of osteoporosis. You should see your doctor regularly to determine if FOSAMAX PLUS D is still right for you.

FOSAMAX PLUS D is not for use in children.

Who should not take FOSAMAX PLUS D?

Do not take FOSAMAX PLUS D if you:

- Have certain problems with your esophagus, the tube that connects your mouth with your stomach
- Cannot stand or sit upright for at least 30 minutes
- Have low levels of calcium in your blood
- Are allergic to FOSAMAX PLUS D or any of its ingredients. A list of ingredients is at the end of this leaflet.

What should I tell my doctor before taking FOSAMAX PLUS D?

Before you start FOSAMAX PLUS D, be sure to talk to your doctor if you:

- Have problems with swallowing
- Have stomach or digestive problems
- Have low blood calcium
- Plan to have dental surgery or teeth removed
- Have kidney problems
- Have sarcoidosis, leukemia, lymphoma. These conditions may cause changes in vitamin D.
- Have been told you have trouble absorbing minerals in your stomach or intestines (malabsorption syndrome)
- Are pregnant, trying to become pregnant or suspect that you are pregnant. If you become pregnant while taking FOSAMAX PLUS D, stop taking it and contact your doctor. It is not known if FOSAMAX PLUS D can harm your unborn baby.
- Are breast-feeding or plan to breast-feed. It is not known if FOSAMAX PLUS D passes into your milk and may harm your baby.

Especially tell your doctor if you take:

- antacids
- aspirin
- Nonsteroidal Anti-Inflammatory (NSAID) medicines

Tell your doctor about all the medicines you take, including prescription and non-prescription medicines, vitamins, and herbal supplements. Certain medicines may affect how FOSAMAX PLUS D works.

Know the medicines you take. Keep a list of them and show it to your doctor and pharmacist each time you get a new medicine.

How should I take FOSAMAX PLUS D tablet?

- Take FOSAMAX PLUS D exactly as your doctor tells you.
- FOSAMAX PLUS D works only if taken on an empty stomach.
- Take 1 dose of FOSAMAX PLUS D 1 time a week, after you get up for the day and before taking your first food, drink, or other medicine.
- Take FOSAMAX PLUS D while you are sitting or standing.
- Take your FOSAMAX PLUS D tablet with a full glass (6-8 oz) of plain water.
- Do not chew or suck on a tablet of FOSAMAX PLUS D.
- Do not take FOSAMAX PLUS D with mineral water, coffee, tea, soda, or juice.
- Do not take FOSAMAX PLUS D at bedtime.

After swallowing FOSAMAX PLUS D, wait at least 30 minutes:

- Before you lie down. You may sit, stand or walk, and do normal activities like reading.
- Before you take your first food or drink except for plain water.
- Before you take other medicines, including antacids, calcium, and other supplements and vitamins.

Do not lie down for at least 30 minutes after you take FOSAMAX PLUS D and after you eat your first food of the day.

If you miss a dose of FOSAMAX PLUS D, do not take it later in the day. Take your missed dose on the next morning after you remember and then return to your normal schedule. Do not take 2 doses on the same day.

If you take too much FOSAMAX PLUS D, call your doctor. Do not try to vomit. Do not lie down.

What are the possible side effects of FOSAMAX PLUS D?

FOSAMAX PLUS D may cause serious side effects.

- See "What is the most important information I should know about FOSAMAX PLUS D?"

The most common side effects of FOSAMAX PLUS D are:

- Stomach area (abdominal) pain
- Heartburn
- Constipation
- Diarrhea
- Upset stomach
- Pain in your bones, joints, or muscles
- Nausea

You may get allergic reactions, such as hives or swelling of your face, lips, tongue, or throat.

Worsening of asthma has been reported.

Tell your doctor if you have any side effect that bothers you or that does not go away.

These are not all the possible side effects of FOSAMAX PLUS D. For more information, ask your doctor or pharmacist.

Call your doctor for medical advice about side effects. You may report side effects to FDA at 1-800-FDA-1088.

How do I store FOSAMAX PLUS D?

- Store FOSAMAX PLUS D at room temperature, 68°F to 77°F (20°C to 25°C).
- Keep FOSAMAX PLUS D away from light.
- Keep FOSAMAX PLUS D package and tablets dry.
- Store FOSAMAX PLUS D in the original package.

Keep FOSAMAX PLUS D and all medicines out of the reach of children.

General information about the safe and effective use of FOSAMAX PLUS D.

Medicines are sometimes prescribed for purposes other than those listed in a Medication Guide. Do not use FOSAMAX PLUS D for a condition for which it was not prescribed. Do not give FOSAMAX PLUS D to other people, even if they have the same symptoms you have. It may harm them.

This Medication Guide summarizes the most important information about FOSAMAX PLUS D. If you would like more information, talk with your doctor. You can ask your doctor or pharmacist for information about FOSAMAX PLUS D that is written for health professionals.

What are the ingredients in FOSAMAX PLUS D?

Active ingredients: alendronate sodium and cholecalciferol (vitamin D3).

Inactive ingredients: cellulose, lactose, medium chain triglycerides, gelatin, croscarmellose sodium, sucrose, colloidal silicon dioxide, magnesium stearate, butylated hydroxytoluene, modified food starch, and sodium aluminum silicate.

Dist. by: Organon LLC, a subsidiary of
ORGANON & Co.,
Jersey City, NJ 07302, USA

For patent information: www.organon.com/our-solutions/patent/

© 2026 Organon group of companies. All rights reserved.

Revised: 2/2026

usmg-og0217a-t-2602r002

This Medication Guide has been approved by the U.S. Food and Drug Administration.

PRINCIPAL DISPLAY PANEL - 70 mg/2800 IU Tablet Blister Pack

FOSAMAX® PLUS D
(alendronate sodium/
cholecalciferol) tablets

70mg
2800IU

Dispense the enclosed
Medication Guide to
each patient.

Each tablet contains
91.37 mg alendronate
sodium (70 mg free acid
equivalent) and 70 mcg
cholecalciferol
equivalent to 2800 IU
vitamin D.

710

4 Tablets

Rx only

USUAL ADULT DOSAGE:
ONE 70 mg/2800 IU TABLET
ONCE WEEKLY

See accompanying circular
for dosage information.

Manuf. for: Organon LLC,
a subsidiary of
ORGANON & Co.,
Jersey City, NJ 07302, USA

By:
Rovi Pharma Industrial Services, S.A.
28805 Alcalá de Henares
Madrid, Spain

Made in Spain

PRINCIPAL DISPLAY PANEL - 70 mg/5600 IU Tablet Blister Pack

FOSAMAX® PLUS D
(alendronate sodium/
cholecalciferol) tablets

70mg
5600IU

Dispense the enclosed
Medication Guide to
each patient.

Each tablet contains
91.37 mg alendronate
sodium (70 mg free acid
equivalent) and 140 mcg
cholecalciferol
equivalent to 5600 IU
vitamin D.

270

4 Tablets

Rx only

USUAL ADULT DOSAGE:
ONE 70 mg/5600 IU
TABLET ONCE WEEKLY

See accompanying circular
for dosage information.

Manuf. for: Organon LLC,
a subsidiary of
ORGANON & Co.,
Jersey City, NJ 07302, USA

By:
Rovi Pharma Industrial Services, S.A.
28805 Alcalá de Henares
Madrid, Spain

Made in Spain